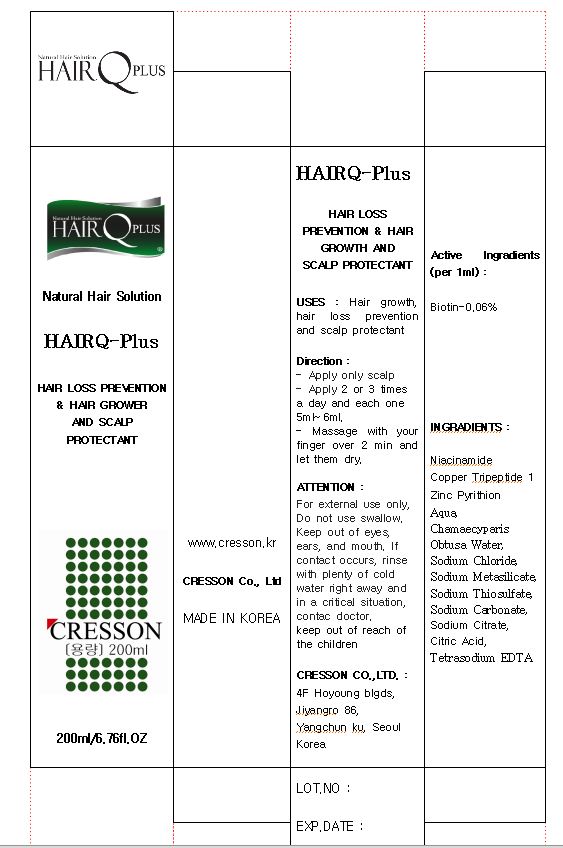 DRUG LABEL: HairQ-Plus
NDC: 49658-4001 | Form: SOLUTION
Manufacturer: Cresson
Category: otc | Type: HUMAN OTC DRUG LABEL
Date: 20120525

ACTIVE INGREDIENTS: BIOTIN 0.06 mL/100 mL
INACTIVE INGREDIENTS: WATER; SODIUM CHLORIDE; SODIUM THIOSULFATE; SODIUM CARBONATE; SODIUM CITRATE; CITRIC ACID MONOHYDRATE; EDETATE SODIUM; NIACINAMIDE; PYRITHIONE ZINC

Drug Facts

active ingredient: biotin

inactive ingredient: niacinamide, water,copper tripeptide, zinc pyrithion, chamaecyparis, obtusa water, sodium chloride, sodium metasilicate, sodium thiosulfate, sodium carbonate, sodium citrate, citric acid, tetrasodium EDTA

PURPOSE

hair growth, hair loss prevention and scalp protectant

keep out of reach of the children

INDICATIONS AND USAGE

- apply only for scalp
- apply 2 or 3 times a day with 5~6ml
- massage with your finger over 2 min and let them dry

WARNINGS

- keep out of eyes, ears and mouth
- if contact occurs, rinse away with plenty of cold water

DOSAGE AND ADMINISTRATION

- for external use only